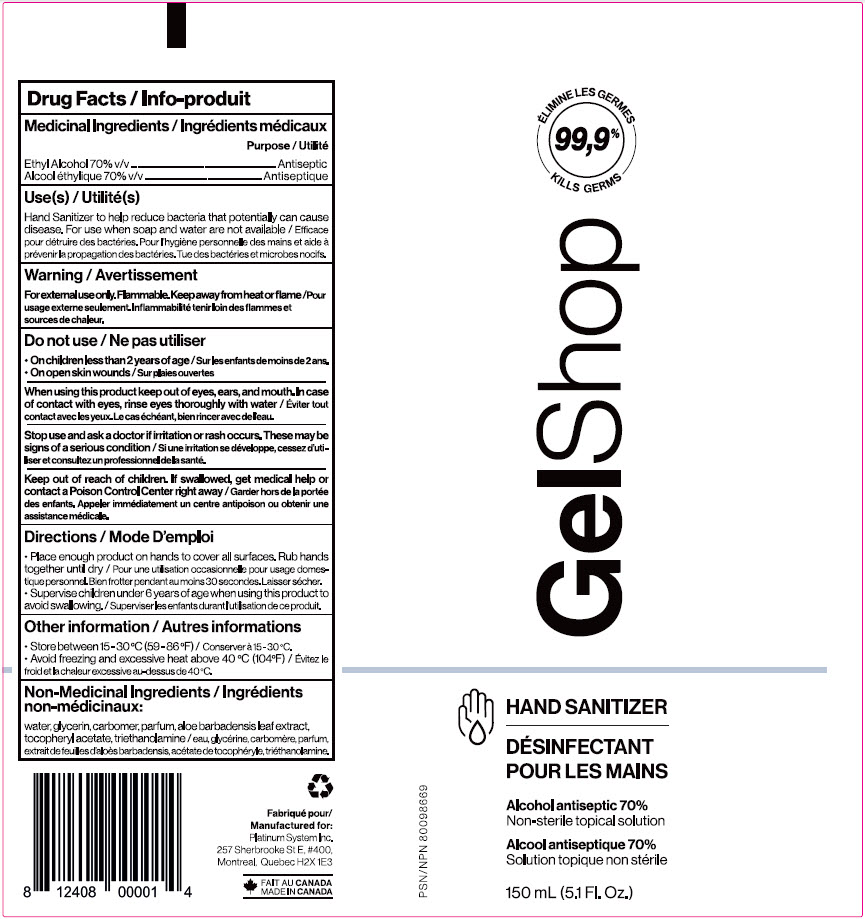 DRUG LABEL: Hand Sanitizer
NDC: 78795-101 | Form: SOLUTION
Manufacturer: Platinum System Inc
Category: otc | Type: HUMAN OTC DRUG LABEL
Date: 20220125

ACTIVE INGREDIENTS: ALCOHOL 70 mL/100 mL
INACTIVE INGREDIENTS: CARBOMER HOMOPOLYMER, UNSPECIFIED TYPE; WATER; .ALPHA.-TOCOPHEROL ACETATE, DL-; ALOE VERA LEAF; TROLAMINE; GLYCERIN

GelShop Hand Sanitizer (Alcohol Antiseptic 70%)
Drug Facts

Medicinal Ingredients

Ethyl Alcohol 70% v/v

Purpose

Antiseptic

Use(s)

Hand Sanitizer to help reduce bacteria that potentially can cause disease. For use when soap and water are not available

Warning

For external use only. Flammable. Keep away from heat or flame

Do not use

- On children less than 2 months of age
- On open skin wounds

When using this product keep out of eyes, ears, and mouth. In case of contact with eyes, rinse eyes thoroughly with water.

Stop use and ask a doctor if irritation or rash occurs. These may be signs of a serious condition.

Keep out of reach of children. If swallowed, get medical help or contact a Poison Control Center right away

Directions

- Place enough product on hands to cover all surfaces. Rub hands together until dry
- Supervise children under 6 years of age when using this product to avoid swallowing

Other information

- Store between 15-30°C (59-86°F)
- Avoid freezing and excessive heat above 40°C (104°F)

Non-Medicinal Ingredients

water, glycerin, carbomer, parfume, aloe barbadensis leaf extract, tocopheryl acetate, triethanolamine

Package Label - Principal Display Panel

150 mL NDC: 71316-101-14

ÉLIMINE LES GERMES
99,9%
KILLS GERMS

GelShop

HAND SANITIZER
DÉSINFECTANT
POUR LES MAINS

Alcohol antiseptic 70%
Non-sterile topical solution

Alcool antiseptique 70%
Solution topique non stérile

150 mL (5.1 Fl. Oz.)